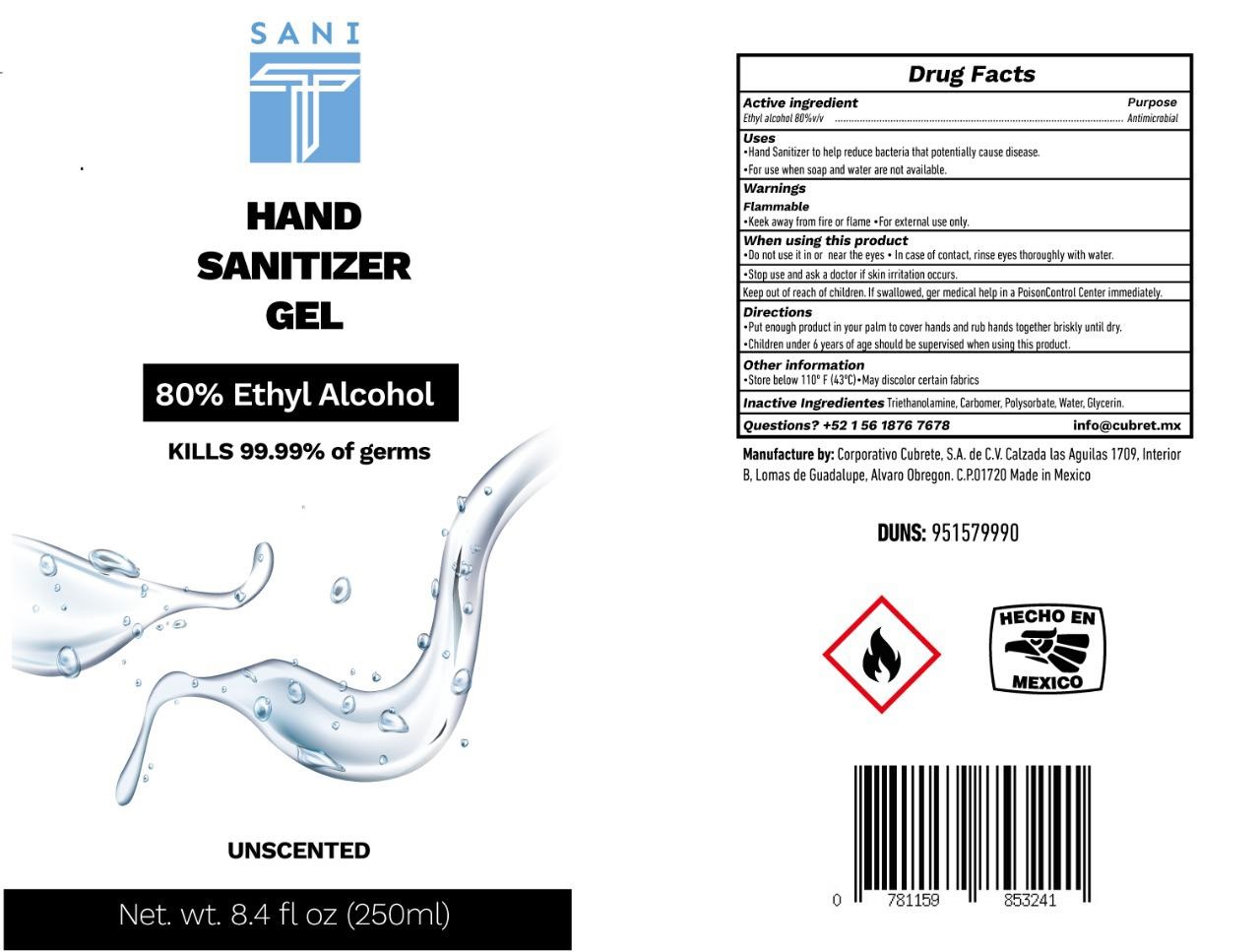 DRUG LABEL: Sani T Hand Sanitizer
NDC: 79410-002 | Form: GEL
Manufacturer: Corporativo Cubrete, S.A. de C.V.
Category: otc | Type: HUMAN OTC DRUG LABEL
Date: 20220104

ACTIVE INGREDIENTS: ALCOHOL 0.8 mL/1 mL
INACTIVE INGREDIENTS: TROLAMINE; CARBOMER HOMOPOLYMER, UNSPECIFIED TYPE; WATER; GLYCERIN

Sani T Hand Sanitizer GEL

Active ingredient

Ethyl alcohol 80% v/v

Purpose

Antimicrobial

Uses

- Hand Sanitizer to help reduce bacteria that potentially cause disease.
- For use when soap and water are not available.

Warnings

Flammable

- Keek away from fire or flame
- For external use only.

When using this product

- Do not use it in or near the eyes
- In case of contact, rinse eyes thoroughly with water.

Stop use and ask a doctor

if skin irritation occurs.

Keep out of reach of children.

If swallowed, ger medical help in a PoisonControl Center immediately.

Directions

- Put enough product in your palm to cover hands and rub hands together briskly until dry.
- Children under 6 years of age should be supervised when using this product.

Other information

- Store below 110° F (43°C)
- May discolor certain fabrics

Inactive Ingredients

Triethanolamine, Carbomer, Polysorbate, Water, Glycerin.

Questions?

+52 1 56 1876 7678 info@cubret.mx